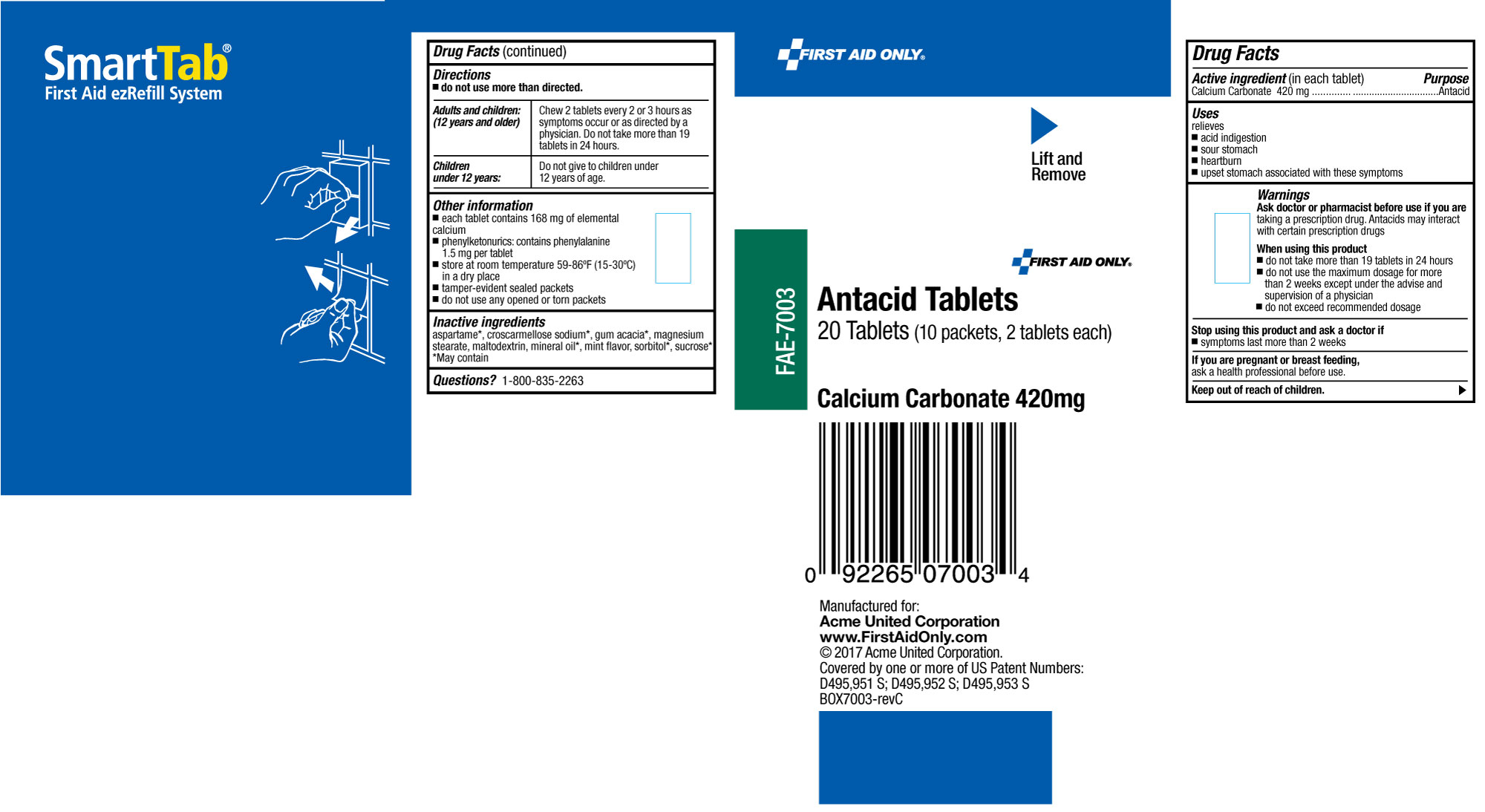 DRUG LABEL: First Aid Only Antacid
NDC: 0924-0287 | Form: TABLET, CHEWABLE
Manufacturer: Acme United Corporation
Category: otc | Type: HUMAN OTC DRUG LABEL
Date: 20241126

ACTIVE INGREDIENTS: CALCIUM CARBONATE 420 mg/1 1
INACTIVE INGREDIENTS: ASPARTAME; CROSCARMELLOSE SODIUM; MAGNESIUM STEARATE; MALTODEXTRIN; MINERAL OIL; SORBITOL

First Aid Only Antacid Tablets

Drug Facts

Active ingredient (in each tablet)

Calcium Carbonate 420 mg

Purpose

Antacid

Uses

For the relief of the following symptoms associated with

- acid indigestion
- sour stomach
- heartburn
- upset stomach associated with these symptoms

Warnings

Ask a doctor or phamacist before use if you are

- taking a prescription drug. Antacids may interact with certain prescription drugs.

When using this product

- do not take more than 19 tablets in 24 hours
- do not use the maximum dosage for more than 2 weeks except under the advise and supervision of a physician
- do not exceed recommended dosage

Stop using this product and ask a doctor if

- symptoms last more than 2 weeks

Keep out of the reach of children.

As with any drug, if you are pregnant or nursing a baby, seek the advice of a health professional before using this product.

If you are pregnant or breast feeding,

ask a health profdessional before use.

Directions

- do not use more than directed

Adults and children: (12 years and older) Chew 2 tablets every 2 or 3 hours as symptoms occur or as directed by a physician. Do not take more than 19 tablets in 24 hours.

Children under 12 years: Do not give to children under 12 years of age.

Other information

- Phenylketonurics: contains phenylalanine 1.5 mg per tablet
- each tablet contains 168 mg of elemental calcium
- store at room temperature 59-86°F (15-30°C) in a dry place
- tamper-evident sealed packets
- do not use any opened or torn packets

Inactive ingredients

aspartame*, croscarmellose sodium*, gum acacia*, magnesium stearate, maltodextrin, mineral oil*, mint flavor, sorbitol*, sucrose*

*may contain

Questions or comments?

Call 1-800-835-2263

First Aid Only Antacid Label